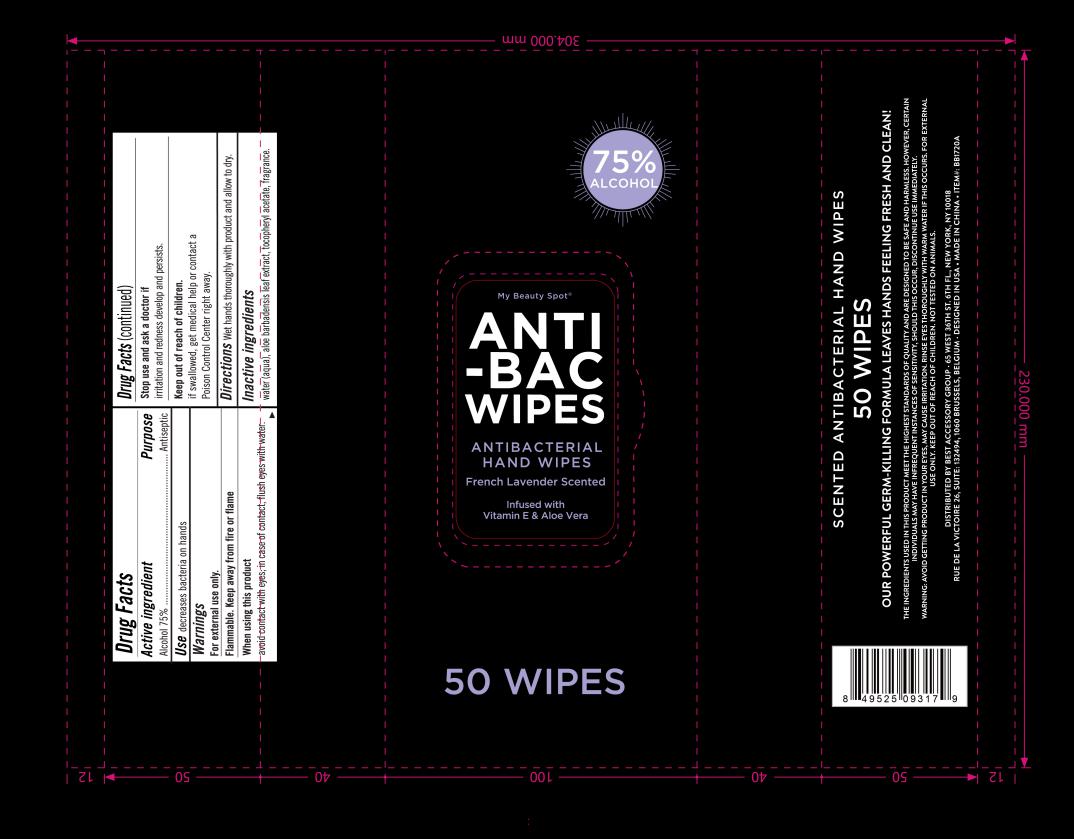 DRUG LABEL: BB1720A ANTIBACTERIAL HAND WIPES FRENCH LAVENDER SCENTED
NDC: 78936-007 | Form: SWAB
Manufacturer: Hangzhou Caring Cleaning Commodity Co.,Ltd
Category: otc | Type: HUMAN OTC DRUG LABEL
Date: 20200707

ACTIVE INGREDIENTS: ALCOHOL 75 g/100 g
INACTIVE INGREDIENTS: ALOE VERA LEAF; ALPHA-TOCOPHEROL ACETATE; WATER; FRAGRANCE LAVENDER & CHIA F-153480

BB1720A ANTIBACTERIAL HAND WIPES FRENCH LAVENDER SCENTED

Active Ingredient(s)

Alcohol 75%

Purpose

Antiseptic

Use

For hand washing to decreases bacteria on skin.

Warnings

For external use only.

Flammable, keep away from fire or flame.

When using this product

Avoid contact with eyes; in case of contact, flush eyes with water

Stop use and ask a doctor if irritation or redness develops and persist for more than 72 hours,

Keep out of reach of children. If swallowed, get medical help or contact a Poison Control Center right away.

Inactive ingredients

Water,Aloe Barbadensis Leaf Extract,Tocopheryl Acetate,Fragrance

Directions

Wet hands thoroughly with product and allow to dry

Package Label - Principal Display Panel

50 POUCH IN 1 PACKAGE NDC: 78936-007-01